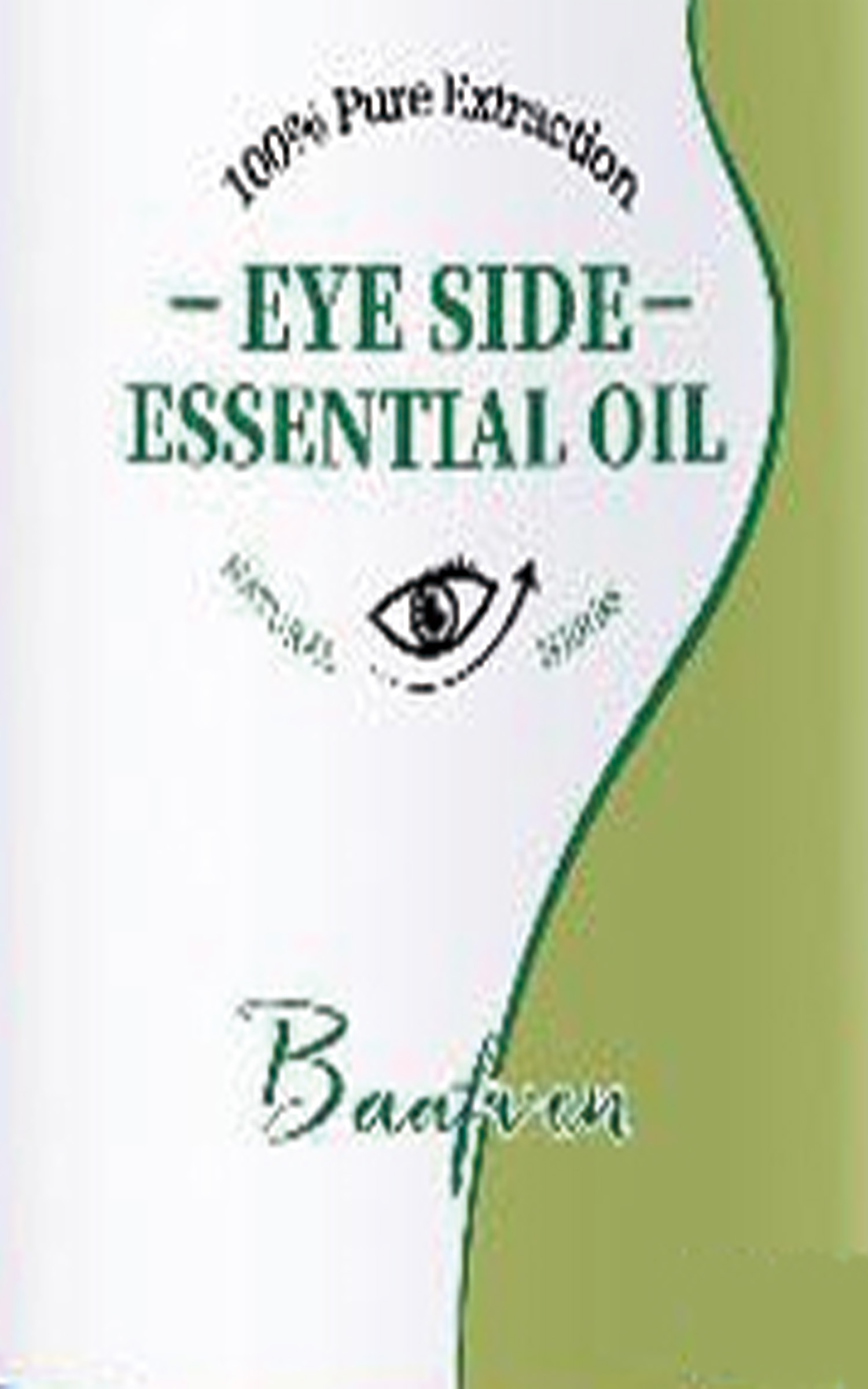 DRUG LABEL: Eye Side Essential Oil
NDC: 84756-371 | Form: LIQUID
Manufacturer: Yiwu Zhixin Trade Co Ltd
Category: otc | Type: HUMAN OTC DRUG LABEL
Date: 20241119

ACTIVE INGREDIENTS: NIACINAMIDE 5 g/100 mL
INACTIVE INGREDIENTS: GLYCERIN; CHLORPHENESIN; PALMITOYL PENTAPEPTIDE-4; SESAME OIL; PALMITOYL TRIPEPTIDE-1

COMPONENTS

Salicylic acid 2%

PURPOSE

wart remover

INDICATIONS AND USAGE

Apply twice daly(moring and night as a man and once as a woman.Afer apicaion, proeed with an acive masage for 3-5 minutes unthe product is fuy absorbed

DOSAGE AND ADMINISTRATION

For external use only.

STOP USE

on broken or irritated scalp

KEEP OUT OF REACH OF CHILDREN

If sxralowed, get medical help or contact a Poison Conirol Cenler ngiht away.

INACTIVE INGREDIENT

Acrylates copolymer, Ethyl acetate